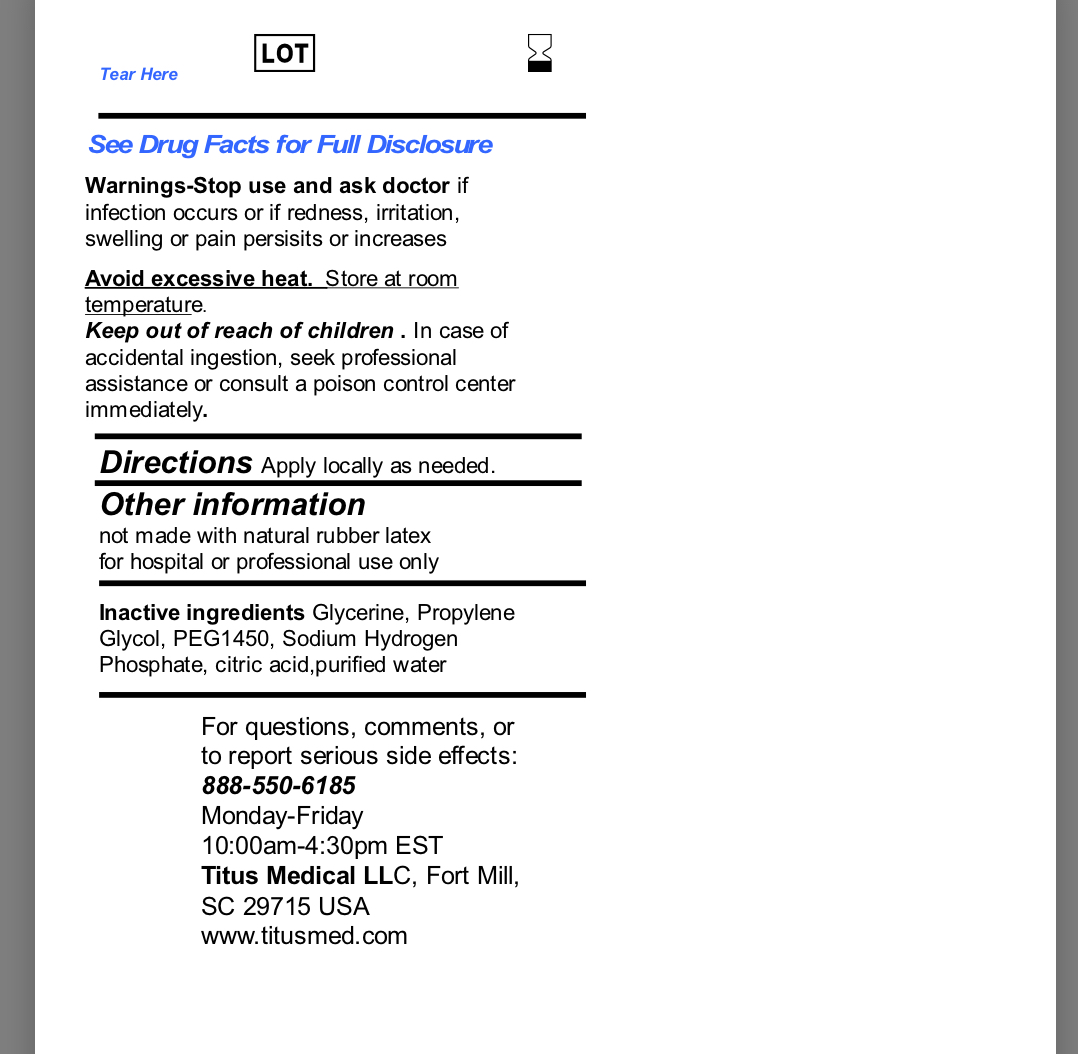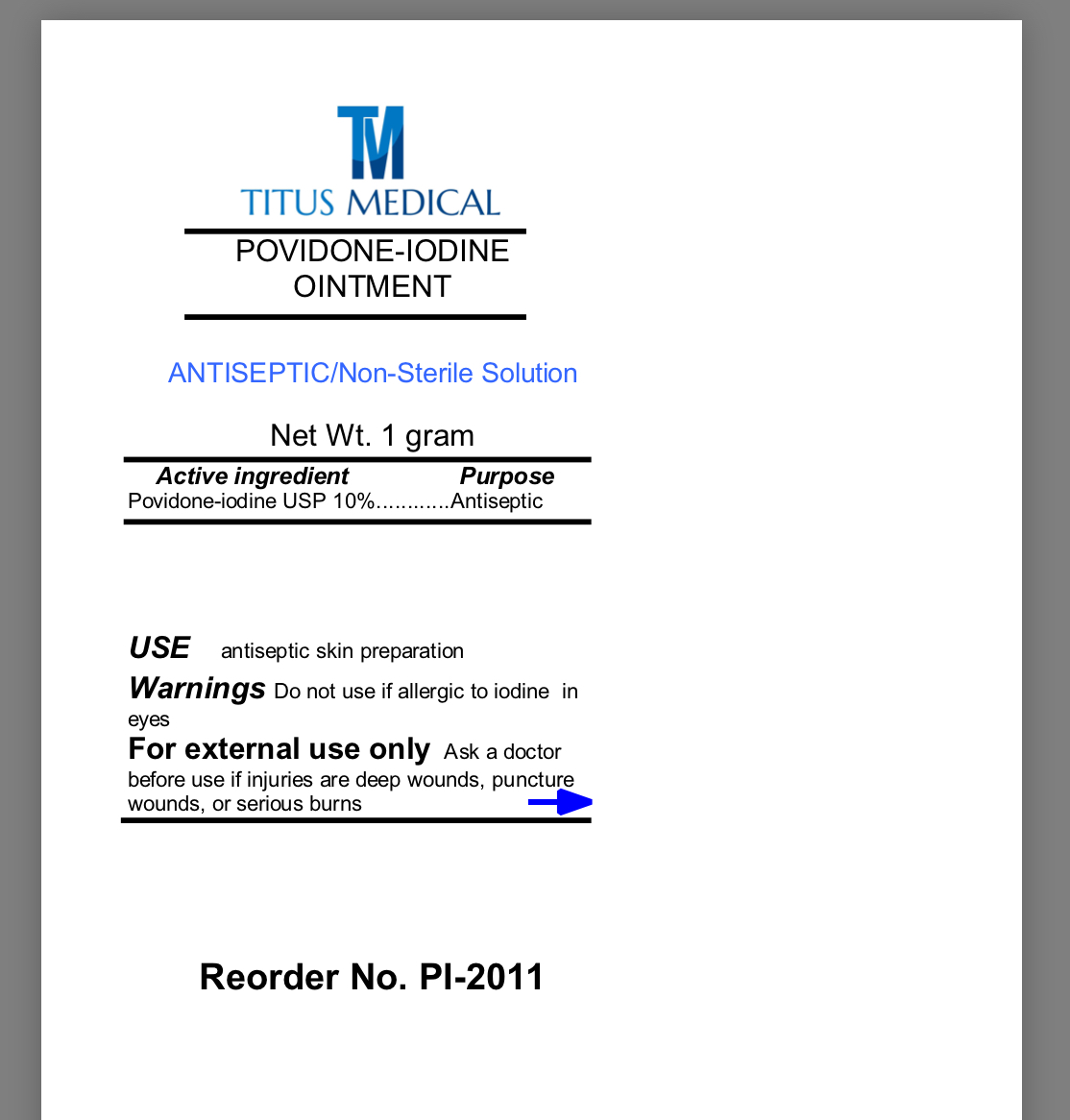 DRUG LABEL: TM Titus Medical Povidone Iodine
NDC: 81526-002 | Form: OINTMENT
Manufacturer: Titus Medical LLC
Category: otc | Type: HUMAN OTC DRUG LABEL
Date: 20250117

ACTIVE INGREDIENTS: POVIDONE-IODINE 1 g/100 g
INACTIVE INGREDIENTS: PROPYLENE GLYCOL; WATER; CITRIC ACID MONOHYDRATE; SODIUM PHOSPHATE, DIBASIC; GLYCERIN

81526-002

Active Ingredient

Povidone-Iodine USP (10%)

Purpose

Antiseptic

Uses

Antiseptic skin preparation

Warnings

For external use only

Do not use if allergic to iodine in the eyes

Keep out of reach of children. In case of accidental ingestion, seek professional assistance or consult a poison control center immediately

Ask a doctor before use if injuries are deep wounds, puncture wounds or serious burns

Stop use and ask a doctor if infection occurs or if redness, irritation, swelling, or pain persists or increases

Directions

Apply locally as need

Other information

- not made with natural rubber latex
- for hospital or professional use only

Inactive Ingredient

Glycerin, Propylene Glycol, PEG 1450, Sodium Hydrogen Phosphate, Citric Acid, Water